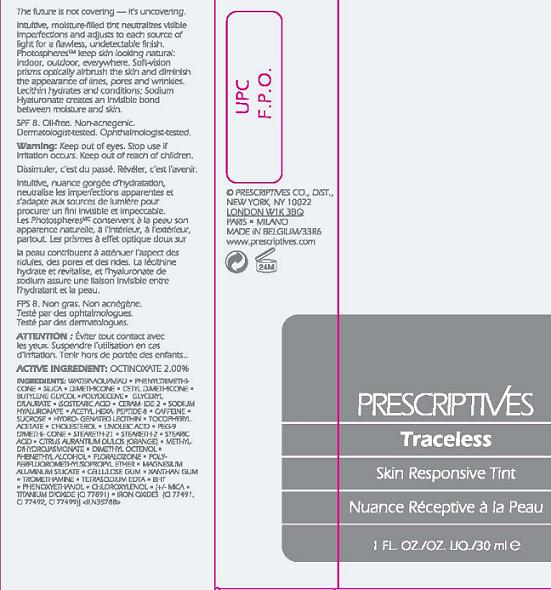 DRUG LABEL: TRACELESS
NDC: 59158-731 | Form: CREAM
Manufacturer: PRESCRIPTIVES INC.
Category: otc | Type: HUMAN OTC DRUG LABEL
Date: 20110405

ACTIVE INGREDIENTS: OCTINOXATE 2.0 mL/100 mL
INACTIVE INGREDIENTS: WATER; SILICON DIOXIDE; DIMETHICONE; BUTYLENE GLYCOL; ISOSTEARIC ACID; HYALURONATE SODIUM; CAFFEINE; SUCROSE; HYDROGENATED SOYBEAN LECITHIN; .ALPHA.-TOCOPHEROL ACETATE, DL-; CHOLESTEROL; LINOLEIC ACID; XANTHAN GUM; PHENOXYETHANOL; FERRIC OXIDE RED; FERRIC OXIDE YELLOW; FERROSOFERRIC OXIDE

ACTIVE INGREDIENT: OCTISALATE 2%

INACTIVE INGREDIENT

WATER [] PHENYL TRIMETHICONE [] SILICA [] DIMETHICONE [] CETYL DIMETHICONE [] BUTYLENE GLYCOL [] POLYDECENE [] GLYCERYL DILAURATE [] ISOSTEARIC ACID [] CERAMIDE 2 [] SODIUM HYALURONATE [] ACETYL HEXAPEPTIDE-8 [] CAFFEINE [] SUCROSE [] HYDROGENATED LECITHIN [] TOCOPHERYL ACETATE [] CHOLESTEROL [] LINOLEIC ACID [] PEG-9 DIMETHICONE [] STEARETH-21 [] STEARETH-2 [] STEARIC ACID [] CITRUS AURANTIUM DULCIS (ORANGE) [] METHYLDIHYDROJASMONATE [] DIMETHYL OCTENOL [] PHENETHYL ALCOHOL [] FLORALOZONE [] POLYPERFLUOROMETHYLISOPROPYL ETHER [] MAGNESIUM ALUMINUM SILICATE [] CELLULOSE GUM [] XANTHAN GUM [] TROMETHAMINE [] TETRASODIUM EDTA [] BHT [] PHENOXYETHANOL [] CHLOROXYLENOL [] [+/- MICA [] TITANIUM DIOXIDE (CI 77891) [] IRON OXIDES (CI 77491, CI 77492, CI 77499)

WARNINGS

WARNING: KEEP OUT OF EYES. STOP USE IF IRRITATION OCCURS. KEEP OUT OF REACH OF CHILDREN.

PACKAGE LABEL

PRINCIPAL DISPLAY PANEL:

PRESCRIPTIVES
TRACELESS
SKIN RESPONSIVE TINT
1 FL OZ./ 30 ML

PRESCIPTIVES DISTR

NY,NY 10022